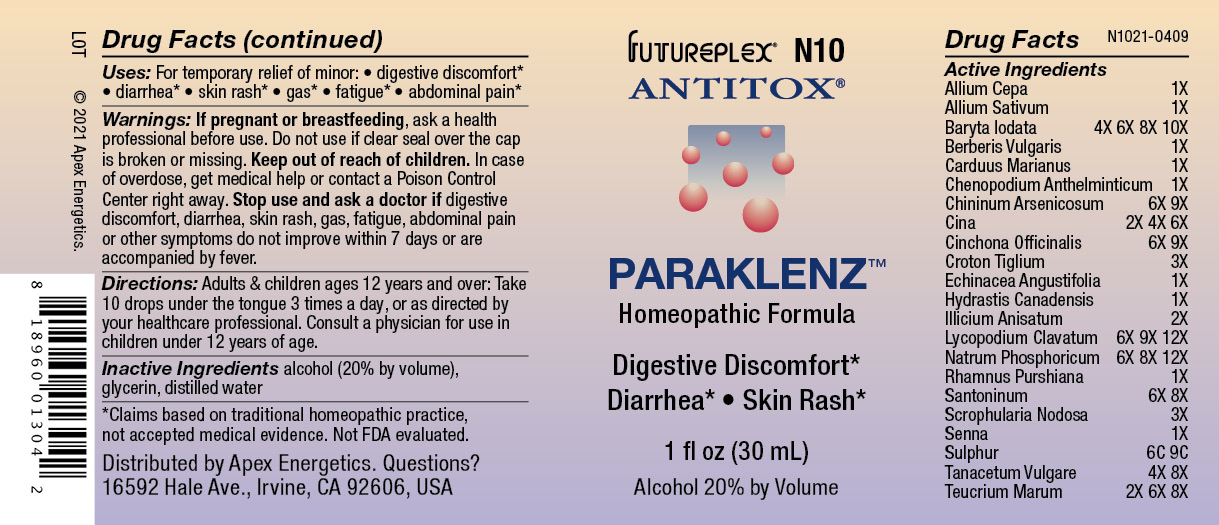 DRUG LABEL: N10
NDC: 63479-1410 | Form: SOLUTION/ DROPS
Manufacturer: Apex Energetics Inc.
Category: homeopathic | Type: HUMAN OTC DRUG LABEL
Date: 20240108

ACTIVE INGREDIENTS: TEUCRIUM MARUM 8 [hp_X]/1 mL; ONION 1 [hp_X]/1 mL; GARLIC 1 [hp_X]/1 mL; SCROPHULARIA NODOSA 3 [hp_X]/1 mL; TANACETUM VULGARE TOP 8 [hp_X]/1 mL; ECHINACEA ANGUSTIFOLIA 1 [hp_X]/1 mL; GOLDENSEAL 1 [hp_X]/1 mL; STAR ANISE 2 [hp_X]/1 mL; FRANGULA PURSHIANA BARK 1 [hp_X]/1 mL; SANTONIN 8 [hp_X]/1 mL; ARTEMISIA CINA FLOWER 6 [hp_X]/1 mL; MILK THISTLE 1 [hp_X]/1 mL; CHENOPODIUM AMBROSIOIDES 1 [hp_X]/1 mL; QUININE ARSENITE 9 [hp_X]/1 mL; CINCHONA OFFICINALIS BARK 9 [hp_X]/1 mL; CROTON TIGLIUM SEED 3 [hp_X]/1 mL; SENNA LEAF 1 [hp_X]/1 mL; SODIUM PHOSPHATE, DIBASIC, HEPTAHYDRATE 12 [hp_X]/1 mL; SULFUR 9 [hp_C]/1 mL; BARIUM IODIDE 10 [hp_X]/1 mL; BERBERIS VULGARIS ROOT BARK 1 [hp_X]/1 mL; LYCOPODIUM CLAVATUM SPORE 12 [hp_X]/1 mL
INACTIVE INGREDIENTS: GLYCERIN; WATER; ALCOHOL

N10

Active Ingredients
Allium Cepa | 1X
Allium Sativum | 1X
Baryta Iodata | 4X 6X 8X 10X
Berberis Vulgaris | 1X
Carduus Marianus | 1X
Chenopodium Anthelminticum | 1X
Chininum Arsenicosum | 6X 9X
Cina | 2X 4X 6X
Cinchona Officinalis | 6X 9X
Croton Tiglium | 3X
Echinacea Angustifolia | 1X
Hydrastis Canadensis | 1X
Illicium Anisatum | 2X
Lycopodium Clavatum | 6X 9X 12X
Natrum Phosphoricum | 6X 8X 12X
Rhamnus Purshiana | 1X
Santoninum | 6X 8X
Scrophularia Nodosa | 3X
Senna | 1X
Sulphur | 6C 9C
Tanacetum Vulgare | 4X 8X
Teucrium Marum | 2X 6X 8X

INDICATIONS AND USAGE

Uses:

For temporary relief of minor:

digestive discomfort*
diarrhea*

skin rash*

gas*

fatigue*

abdominal pain*

*Claims based on traditional homeopathic practice, not accepted medical evidence. Not FDA evaluated.

Warnings:

PREGNANCY OR BREAST FEEDING

If pregnant or breastfeeding, ask a health professional before use.

Do not use if clear seal over the cap is broken or missing.

Keep out of reach of children. In case of overdose, get medical help or contact a Poison Control Center right away.

Stop use and ask a doctor if digestive discomfort, diarrhea, skin rash, gas, fatigue, abdominal pain or other symptoms do not improve within 7 days or are accompanied by fever.

Directions:

Adults & children ages 12 years and over: Take 10 drops under the tongue 3 times a day, or as directed by your healthcare professional. Consult a physician for use in children under 12 years of age.

Inactive Ingredients

alcohol (20% by volume), glycerin, distilled water

Distributed by Apex Energetics. Questions?

16592 Hale Ave., Irvine, CA 92606, USA

PACKAGE LABEL

FUTUREPLEX® N10

ANTITOX®

PARAKLENZ™

Homeopathic Formula

Digestive Discomfort*

Diarrhea* Skin Rash*

1 fl oz (30 mL)

Alcohol 20% by Volume